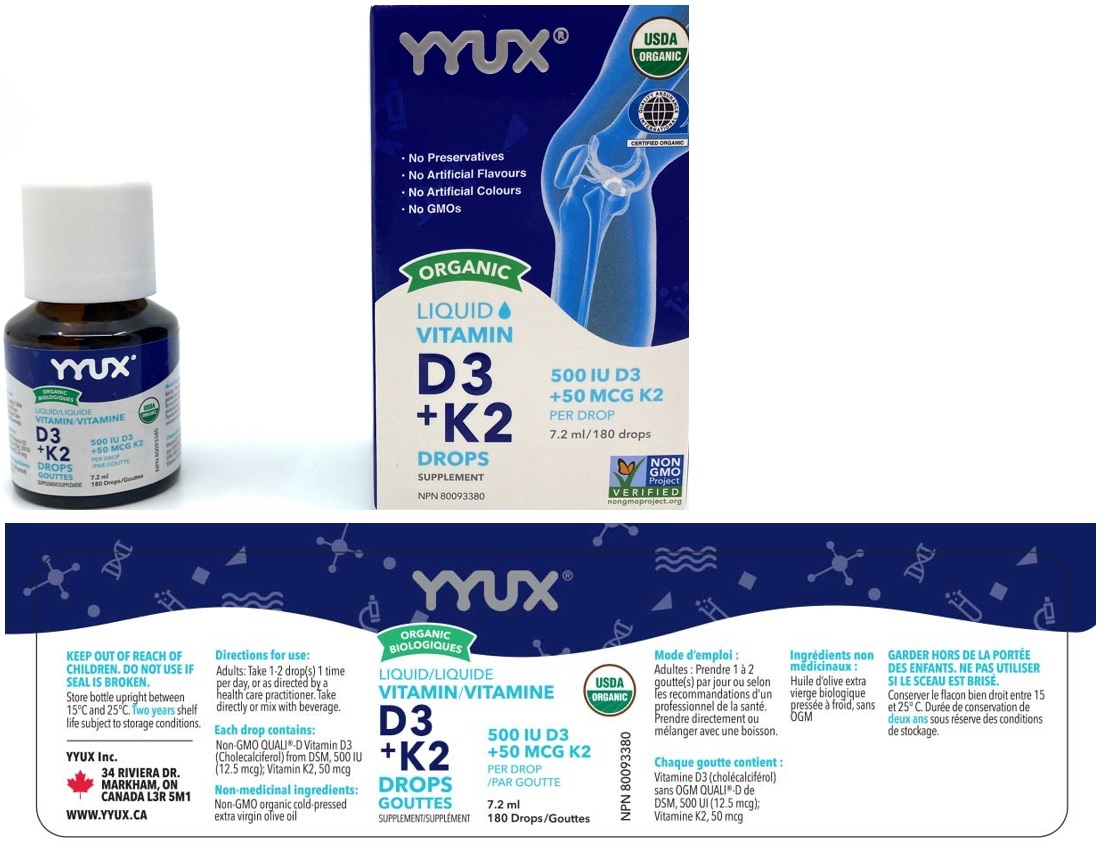 DRUG LABEL: YYUX Organic Liquid Vitamin D3 plus K2 Drops
NDC: 81303-500 | Form: SOLUTION/ DROPS
Manufacturer: Yyux Inc
Category: other | Type: DIETARY SUPPLEMENT
Date: 20201224

ACTIVE INGREDIENTS: CHOLECALCIFEROL 12.5 ug/0.04 mL; MENAQUINONE 7 50 ug/0.04 mL
INACTIVE INGREDIENTS: OLIVE OIL

YYUX® ORGANIC LIQUID VITAMIN D3 + K2 DROPS SUPPLEMENT

Active Ingredient (per drop)
Vitamin D3 (Cholecalciferol) 500IU (12.5mcg)
Vitamin K2 50 mcg

Supplement Facts
Serving Size: 1 drop
Serving Per Container: 180
Amount Per Serving | DV%
Calories 0
Total Fat 0 g | <1%
Cholesterol 0 mg | 0%
Vitamin D3 (Cholecalciferol) 12.5 mcg (500IU) | 83%
Vitamin k2 50mcg | 47.6%
Other ingredients: Olive Oil

Non-medicinal ingredients: Non-GMO organic cold-pressed extra virgin olive oil

Warnings:

KEEP OUT OF REACH OF CHILDREN. DO NOT USE IF SEAL IS BROKEN.

Storage:

Store bottle upright between 15°C and 25°C. Two years shelf life subject to storage conditions.

Directions for use:

Adults: Take 1-2 drop(s) 1 time per day, or as directed by a health care practitioner. Take directly or mix with beverage.

A dropper supplied.

HEALTH CLAIM

Helps in the development and maintenance of bones and teeth. Helps in the absorption and use of calcium and phosphorus. Helps with immune function.

Each drop contains: Non-GMO QUALI®-D Vitamin D3 (Cholecalciferol) from DSM, 500 IU (12.5 mcg); Vitamin K2, 50 mcg

USDA ORGANIC

QUALITY ASSURANCE INTERNATIONAL

CERTIFIED ORGANIC

NON GMO Project VERIFIED

nongmoproject.org

• No Preservatives

• No Artificial Flavours

• No Artificial Colours

• No GMOs
YYUX Inc.
34 RIVIERA DR.
MARKHAM, ON
CANADA L3R 5M1
WWW.YYUX.CA